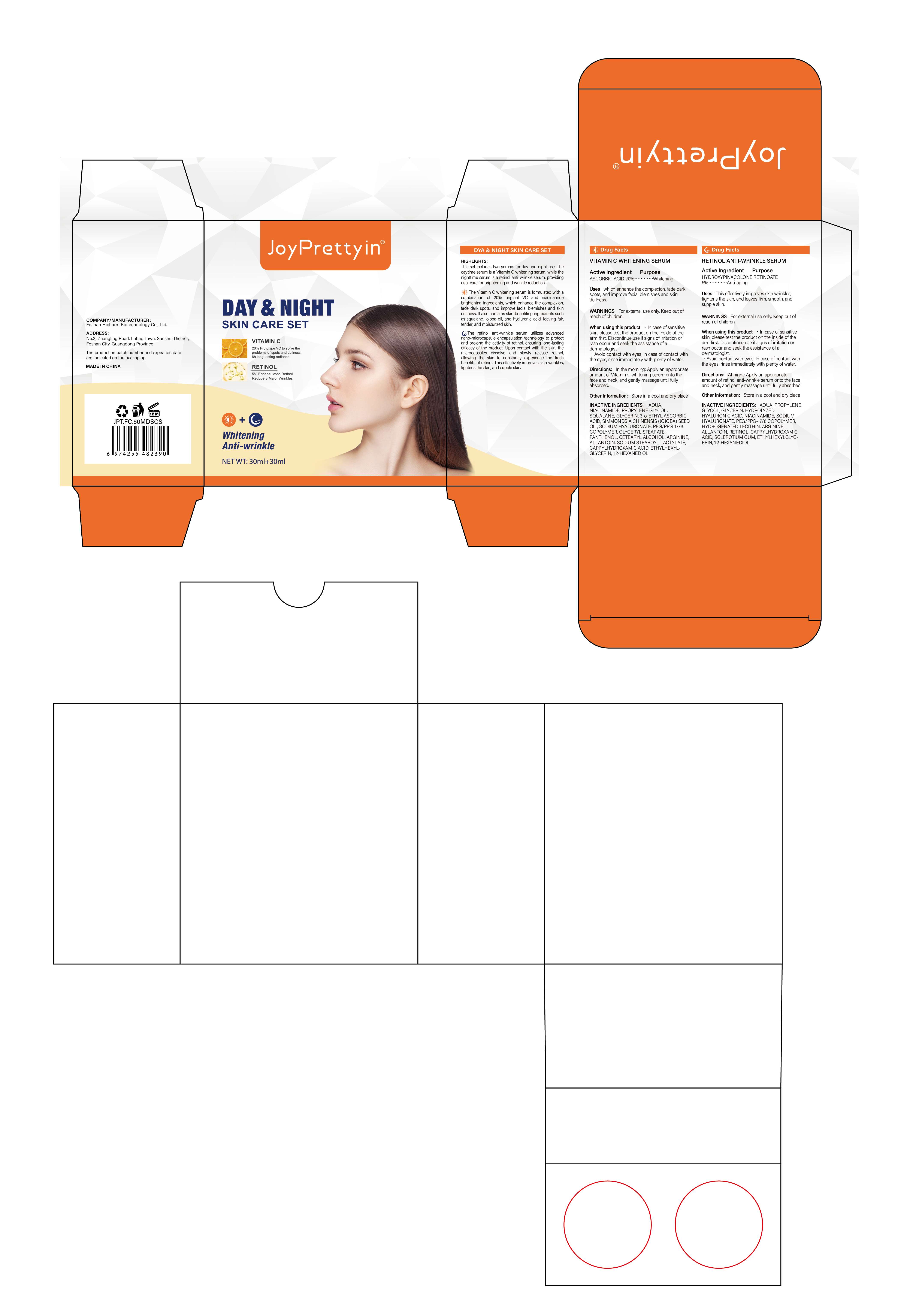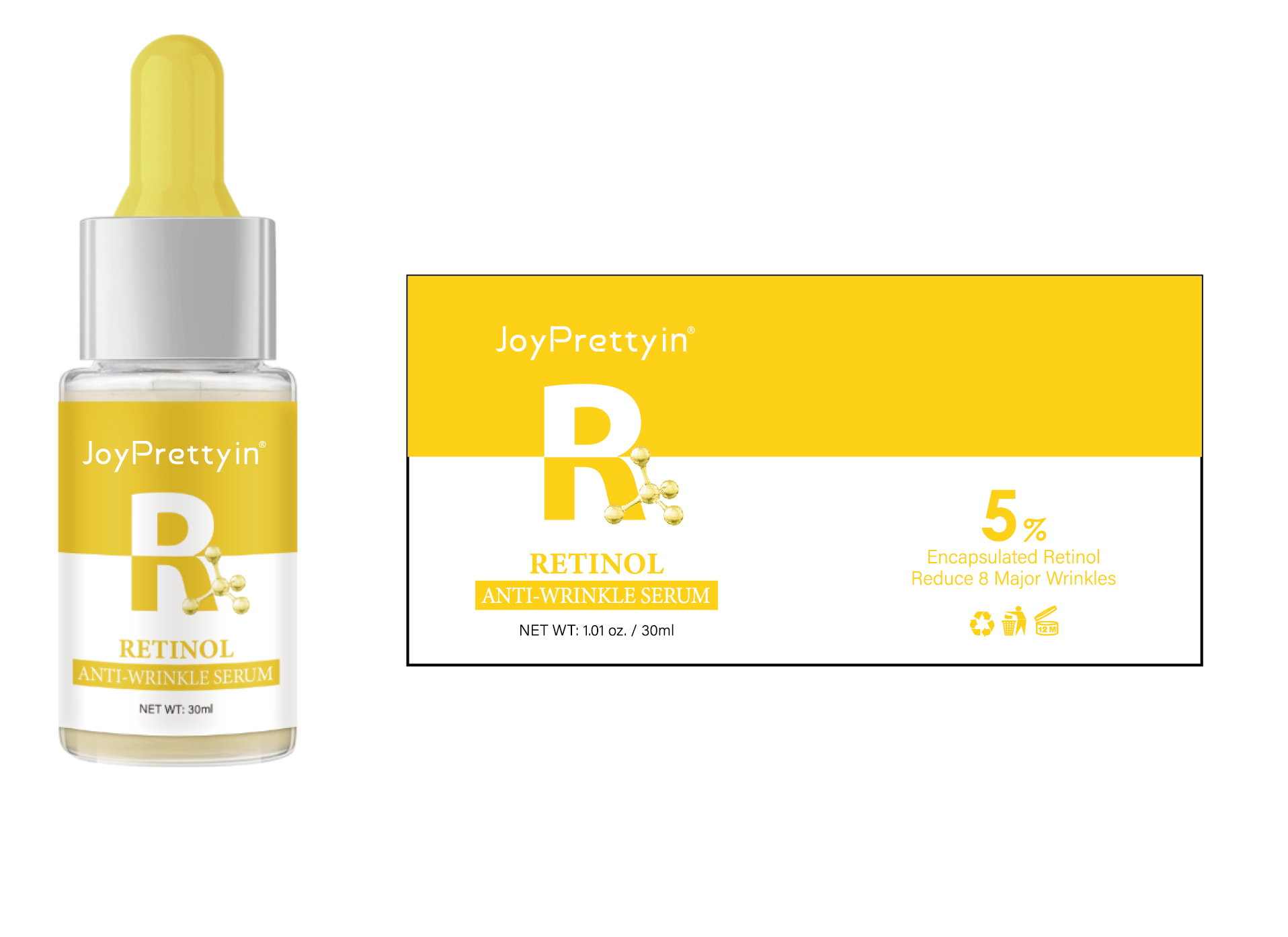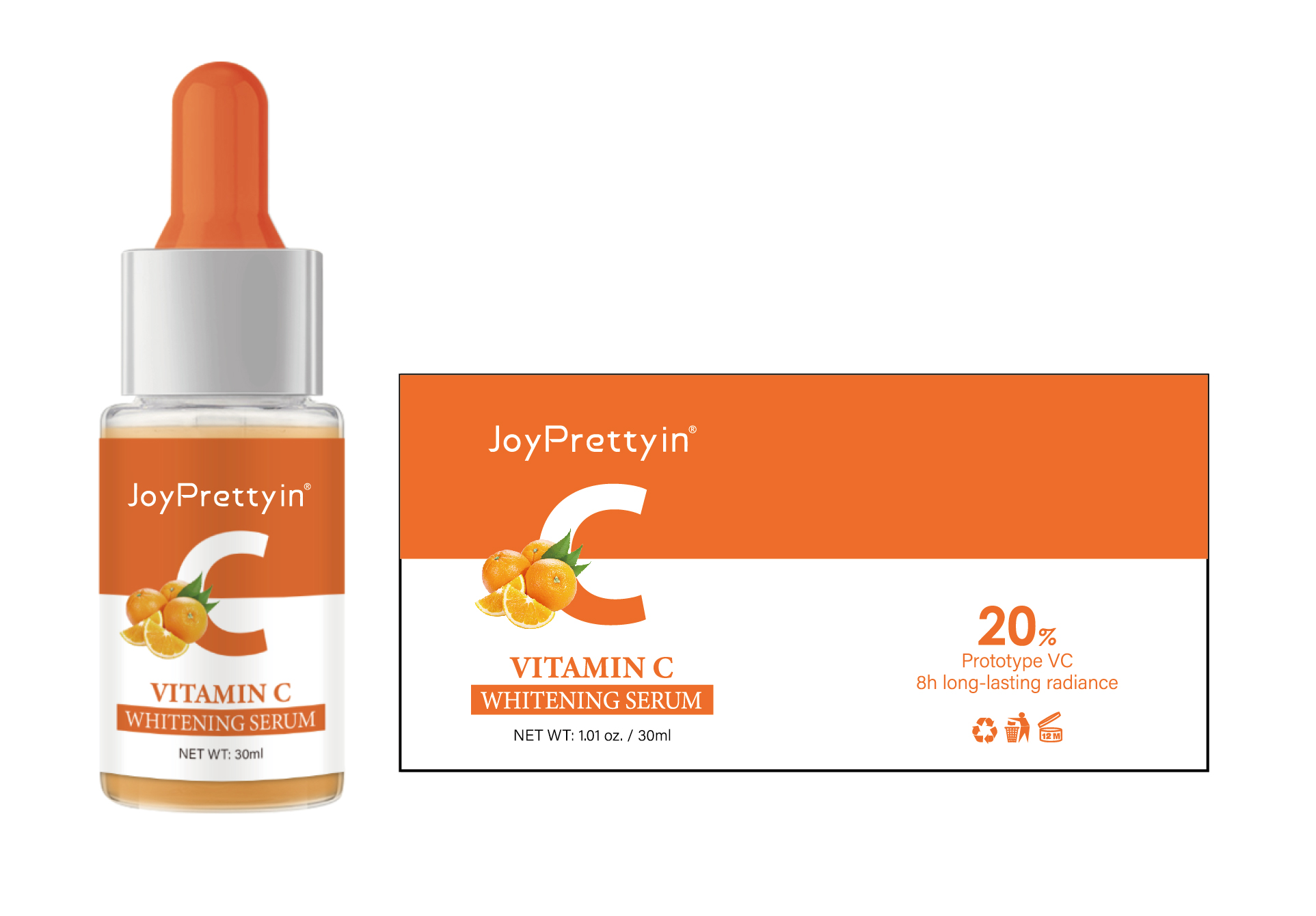 DRUG LABEL: JoyPrettyin RETINOL ANTI-WRINKLE SERUM
NDC: 84186-005 | Form: LIQUID
Manufacturer: Guangzhou Bonnieco Cosmetics Co., Ltd
Category: otc | Type: HUMAN OTC DRUG LABEL
Date: 20240319

ACTIVE INGREDIENTS: HYDROXYPINACOLONE RETINOATE 5 g/100 mL
INACTIVE INGREDIENTS: ALLANTOIN; HYALURONIC ACID; HYALURONATE SODIUM; GLYCERIN; NIACINAMIDE; ARGININE; RETINOL; WATER; ETHYLHEXYLGLYCERIN; 1,2-HEXANEDIOL; CLAVICEPS PURPUREA SCLEROTIUM; LECITHIN, SOYBEAN; CAPRYLHYDROXAMIC ACID; PEG/PPG-17/6 COPOLYMER; PROPYLENE GLYCOL

84186-005 84186-006

Active Ingredient

30ML: JoyPrettyin RETINOL ANTI-WRINKLE SERUM

HYDROXYPINACOLONE RETINOATE 5%

30ML:JoyPrettyin VITAMIN C WHITENING SERUM

ASCORBIC ACID 20%

Purpose

This effectively improves skin wrinkles, tightens the skin, and leaves firm, smooth, and supple skin.

Use

At night: Apply an appropriate amount of retinol anti-wrinkle serum onto the face and neck, and gently massage until fully absorbed.

Warnings

CAUTIONS:
For external use only. Keep out of reach of children. Avoid contact with eyes. Discontinue use if signs of irritation or rash occur. Store in a cool and dry place.

Do not use

If discomfort arises, please immediately stop using the product and seek the assistance of a dermatologist.

When Using

In case of sensitive skin, please test the product on the inside of the arm first.
In case of contact with the eyes, rinse immediately with plenty of water.

Stop Use

If discomfort arises, please immediately stop using the product and seek the assistance of a dermatologist.

Keep Oot Of Reach Of Children

If swallowed, get medical help or contact a poison control center right away.

Directions

At night: Apply an appropriate amount of retinol anti-wrinkle serum onto the face and neck, and gently massage until fully absorbed.

Inactive ingredients

30ML: JoyPrettyin RETINOL ANTI-WRINKLE SERUM

AQUA, PROPYLENE GLYCOL, PEG/PPG-17/6 COPOLYMER, HYDROGENATED LECITHIN, ARGININE, ALLANTOIN, CAPRYLHYDROXAMIC ACID, SCLEROTIUM GUM, ETHYLHEXYLGLYCERIN, 1,2-HEXANEDIOL

30ML:JoyPrettyin VITAMIN C WHITENING SERUM

AQUA, NIACINAMIDE, PROPYLENE GLYCOL, SQUALANE, GLYCERIN, 3-o-ETHYL ASCORBIC ACID, SIMMONDSIA CHINENSIS (JOJOBA) SEED OIL, SODIUM HYALURONATE, PEG/PPG-17/6 COPOLYMER, GLYCERYL STEARATE, PANTHENOL, CETEARYL ALCOHOL, ARGININE, ALLANTOIN, SODIUM STEAROYL LACTYLATE, CAPRYLHYDROXAMIC ACID, ETHYLHEXYLGLYCERIN, 1,2-HEXANEDIOL